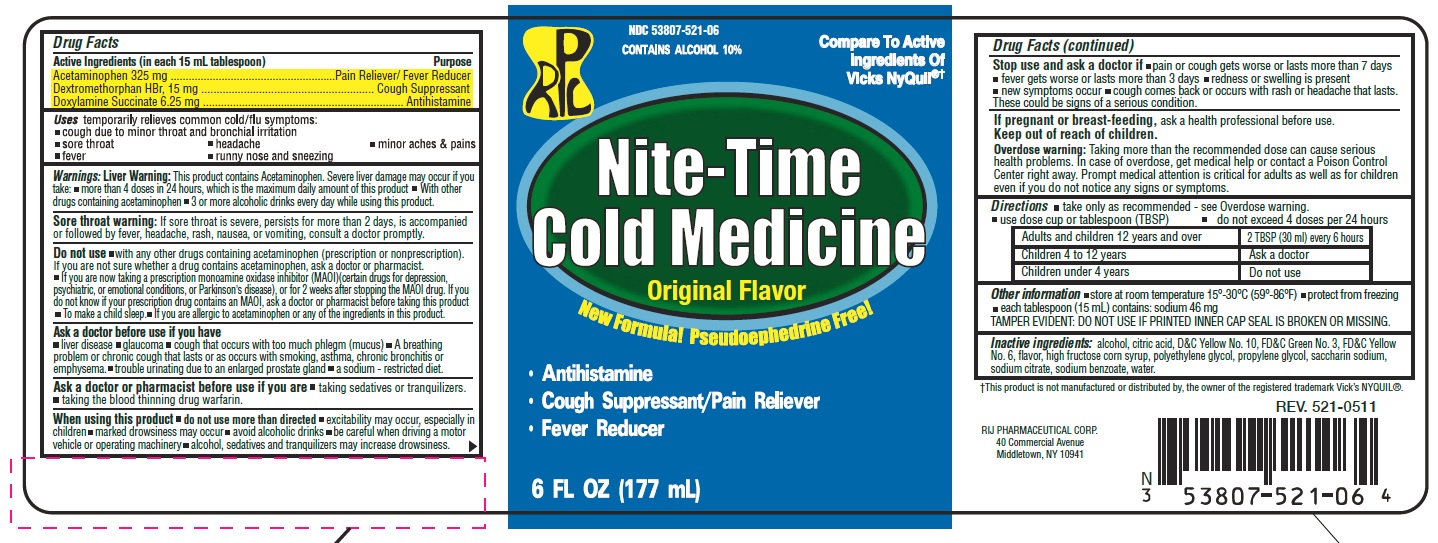 DRUG LABEL: Nite Time
NDC: 53807-521 | Form: LIQUID
Manufacturer: Rij Pharmaceutical Corporation
Category: otc | Type: HUMAN OTC DRUG LABEL
Date: 20180430

ACTIVE INGREDIENTS: Acetaminophen 325 mg/15 mL; Dextromethorphan Hydrobromide 15 mg/15 mL; Doxylamine succinate 6.25 mg/15 mL
INACTIVE INGREDIENTS: alcohol; citric acid monohydrate; D&C Yellow No. 10; FD&C Green No. 3; FD&C Yellow No. 6; high fructose corn syrup; polyethylene glycols; propylene glycol; water; saccharin sodium; sodium benzoate; sodium citrate

Drug Facts

ACTIVE INGREDIENT

Active ingredients (in each 15 mL tablespoon) | Purpose
Acetaminophen 325 mg | Pain reliever/fever reducer
Dextromethorphan HBr, 15 mg | Cough suppressant
Doxylamine succinate 6.25 mg | Antihistamine

Uses

temporarily relieves common cold/flu symptoms:

- cough due to minor throat and bronchial irritation
- sore throat
- headache
- minor aches & pains
- fever
- runny nose and sneezing

Warnings

Liver warning

This product contains acetaminophen. Severe liver damage may occur if you take

- more than 4 doses in 24 hours, which is the maximum daily amount for this product
- with other drugs containing acetaminophen
- 3 or more alcoholic drinks every day while using this product

Sore throat warning

If sore throat is severe, persists for more than 2 days, is accompanied or followed by fever, headache, rash, nausea, or vomiting, consult a doctor promptly.

Do not use

- with any other drug containing acetaminophen (prescription or nonprescription). If you are not sure whether a drug contains acetaminophen, ask a doctor or pharmacist.
- if you are now taking a prescription monoamine oxidase inhibitor (MAOI) (certain drugs for depression, psychiatric or emotional conditions, or Parkinson's disease), or for 2 weeks after stopping the MAOI drug. If you do not know if your prescription drug contains an MAOI, ask a doctor or pharmacist before taking this product.
- to make a child sleep
- if you are allergic to acetaminophen or any of the ingredients in this product.

Ask a doctor before use if you have

- liver disease
- glaucoma
- cough that occurs with too much phlegm (mucus)
- A breathing problem or chronic cough that lasts or as occurs with smoking, asthma, chronic bronchitis or emphysema
- trouble urinating due to enlarged prostate gland
- a sodium-restricted diet

Ask a doctor or pharmacist before use if you are

- taking sedatives or tranquilizers
- taking the blood thinning drug warfarin

When using this product

- do not use more than directed
- excitability may occur, especially in children
- marked drowsiness may occur
- avoid alcoholic drinks
- be careful when driving a motor vehicle or operating machinery
- alcohol, sedatives, and tranquilizers may increase drowsiness

Stop use and ask a doctor if

- pain or cough gets worse or lasts more than 7 days
- fever gets worse or lasts more than 3 days
- redness or swelling is present
- new symptoms occur
- cough comes back or occurs with rash or headache that lasts.
  These could be signs of a serious condition.

PREGNANCY OR BREAST FEEDING

If pregnant or breast-feeding, ask a health professional before use.

Keep out of reach of children.

Overdose warning

Taking more than the recommended dose can cause serious health problems. In case of overdose, get medical help or contact a Poison Control Center right away. Prompt medical attention is critical for adults as well as for children even if you do not notice any signs or symptoms.

Directions

- take only as recommended - see Overdose warning
- use dose cup or tablespoon (TBSP)
- do not exceed 4 doses per 24 hrs

Adults and children 12 years and over | 2 TBSP (30 ml) every 6 hrs
Children 4 to 12 years | Ask a doctor
Children under 4 years | Do not use

Other information

- store at room temperature 15º - 30ºC (59º - 86ºF)
- protect from freezing.
- each tablespoon (15 mL) contains: sodium 46 mg
- TAMPER EVIDENT: DO NOT USE IF PRINTED INNER CAP SEAL IS BROKEN OR MISSING

Inactive ingredients

alcohol, citric acid, D&C Yellow No. 10, FD&C Green No. 3, FD& C Yellow No. 6, flavor, high fructose corn syrup, polyethylene glycol, propylene glycol, saccharin sodium, sodium citrate, sodium benzoate, water